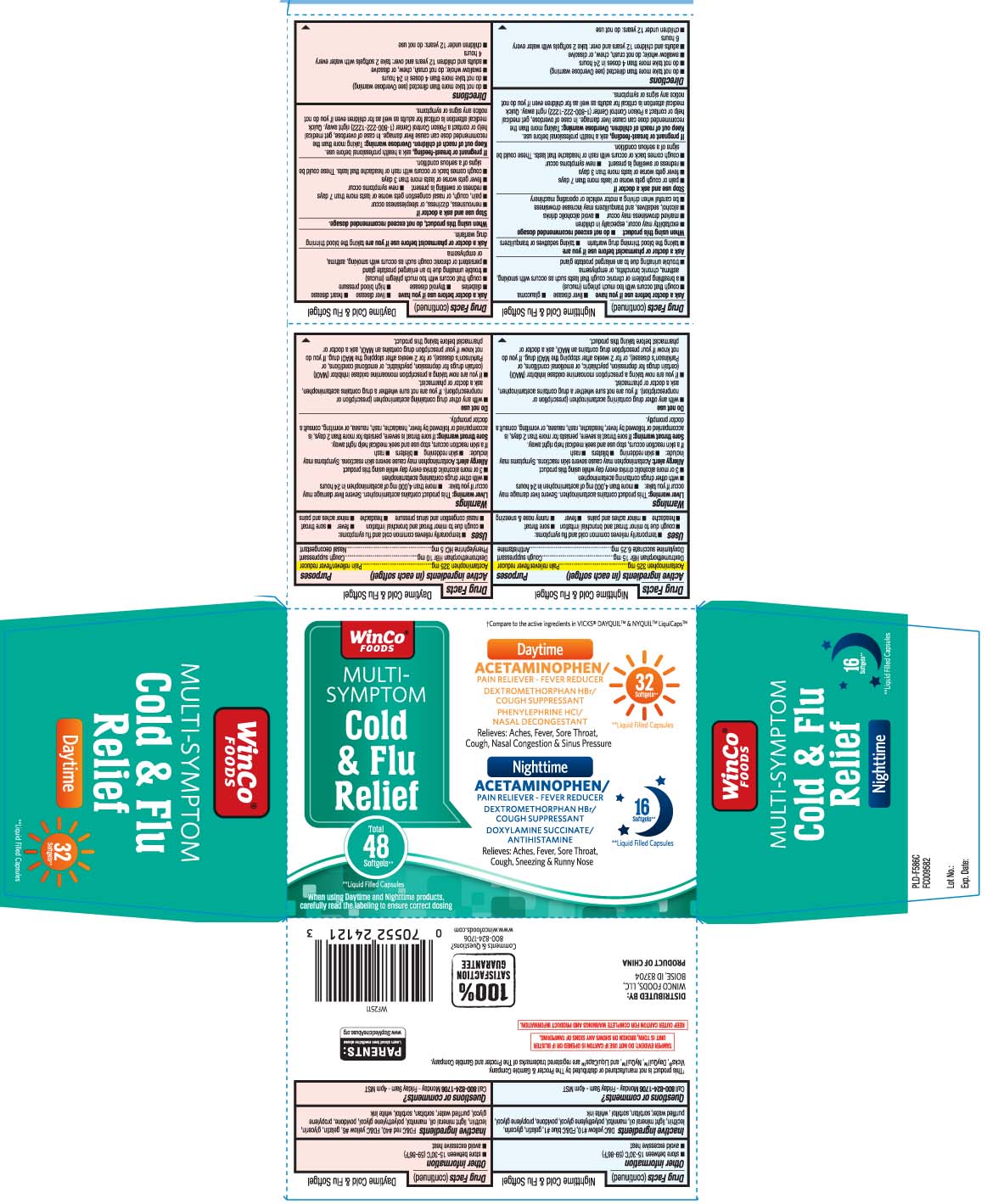 DRUG LABEL: Daytime Nighttime Cold Flu Relief
NDC: 67091-393 | Form: KIT | Route: ORAL
Manufacturer: WinCo Foods, LLC
Category: otc | Type: HUMAN OTC DRUG LABEL
Date: 20260105

ACTIVE INGREDIENTS: ACETAMINOPHEN 325 mg/1 1; DEXTROMETHORPHAN HYDROBROMIDE 15 mg/1 1; DOXYLAMINE SUCCINATE 6.25 mg/1 1; ACETAMINOPHEN 325 mg/1 1; DEXTROMETHORPHAN HYDROBROMIDE 10 mg/1 1; PHENYLEPHRINE HYDROCHLORIDE 5 mg/1 1
INACTIVE INGREDIENTS: D&C YELLOW NO. 10; FD&C BLUE NO. 1; GELATIN; GLYCERIN; POLYETHYLENE GLYCOL, UNSPECIFIED; POVIDONE; PROPYLENE GLYCOL; WATER; SORBITAN; SORBITOL; MANNITOL; LECITHIN, SOYBEAN; LIGHT MINERAL OIL; FD&C YELLOW NO. 6; GELATIN; GLYCERIN; POLYETHYLENE GLYCOL, UNSPECIFIED; POVIDONE; PROPYLENE GLYCOL; WATER; SORBITAN; SORBITOL; MANNITOL; FD&C RED NO. 40; LECITHIN, SOYBEAN; LIGHT MINERAL OIL

DRUG FACTS

Active ingredients for Daytime (in each softgel)

Acetaminophen 325 mg

Dextromethorphan HBr 10 mg

Phenylephrine HCl 5 mg

Active ingredients for Nighttime (in each softgel)

Acetaminophen 325 mg

Dextromethorphan HBr 15 mg

Doxylamine succinate 6.25 mg

Purpose for Daytime

Pain reliever/fever reducer

Cough suppressant

Nasal decongestant

Purpose for Nighttime

Pain reliever/fever reducer

Cough suppressant

Antihistamine

Uses

DAYTIME

- temporarily relieves common cold and flu symptoms
  - cough due to minor throat and bronchial irritation
  - nasal congestion and sinus pressure
  - headache
  - minor aches and pains
  - fever
  - sore throat

NIGHTTIME

- temporarily relieves common cold and flu symptoms
  - cough due to minor throat and bronchial irritation
  - sore throat
  - headache
  - minor aches and pains
  - fever
  - runny nose and sneezing

Warnings

DAYTIME

Liver warning: These products contain acetaminophen. Severe liver damage may occur if you take:

- more than 4,000 mg of acetaminophen in 24 hours
- with other drugs containing acetaminophen
- 3 or more alcoholic drinks every day while using these products

Allergy alert: Acetaminophen may cause severe skin reactions. Symptoms may include:

- skin reddening
- blisters
- rash

If a skin reaction occurs, stop use and seek medical help right away

Sore throat warning: If sore throat is severe, persists for more than 2 days, is accompanied or followed by fever, headache, rash, nausea, or vomiting, consult a doctor promptly.

NIGHTTIME

Liver warning: This product contain acetaminophen. Severe liver damage may occur if you take:

- more than 4,000 mg of acetaminophen in 24 hours
- with other drugs containing acetaminophen
- 3 or more alcoholic drinks every day while using this product

Alergy alert: Acetaminophen may cause severe skin reactions. Symptoms may include:

- skin reddening
- blisters
- rash

If a skin reaction occurs, stop use and seek medical help right away

Sore throat warning: If sore throat is severe, persists for more than 2 days, is accompanied or following by fever, headache, rash, nausea, vomiting, consult a doctor promptly.

Do not use

DAYTIME

- with any other drug containing acetaminophen (prescription or nonprescription). If you are not sure whether a drug contains acetaminophen, ask a doctor or pharmacist.
- if you are now taking a prescription monoamine oxidase inhibitor (MAOI) (certain drugs for depression, psychiatric or emotional conditions, or Parkinson’s disease), or for 2 weeks after stopping the MAOI drug. If you do not know if your prescription drug contains an MAOI, ask a doctor or pharmacist before taking this product.

NIGHTTIME

- with any other drug containing acetaminophen (prescription or nonprescription). If you are not sure whether a drug contains acetaminophen, ask a doctor or pharmacist.
- If you are now taking a prescription monoamine oxidase inhibitor (MAOI) (certain drugs for depression, psychiatric, or emotional conditions,or Parkinson's disease, or for 2 weeks after stopping the MAOI drug. If you do not know if your prescription drug contains an MAOI, ask a doctor or pharmacist before taking this product.

Ask a doctor before use if you have

DAYTIME

- liver disease
- heart disease
- diabetes
- thyroid disease
- high blood pressure
- cough that occurs with too much phlegm (mucus)
- trouble urinating due to an enlarged prostate gland
- persistent or chronic cough such as occurs with smoking, asthma, or emphysema

NIGHTTIME

- liver disease
- glaucoma
- cough that occurs with too much phlegm (mucus)
- a breathing problem or chronic cough such as occurs with smoking, asthma, chronic bronchitis, or emphysema
- trouble urinating due to an enlarged prostate gland

Ask a doctor or pharmacist before use if you are

DAYTIME

taking the blood thinning drug warfarin

NIGHTTIME

- taking the blood thinning drug warfarin
- taking sedatives or tranquilizers

When using this product,

DAYTIME

do not exceed recommended dosage

NIGHTTIME

- do not exceed recommended dosage
- excitability may occur, especially in children
- marked drowsiness may occur
- avoid alcoholic drinks
- alcohol, sedatives, and tranquilizers may increase drowsiness
- be careful when driving a motor vehicle or operating machinery

Stop use and ask a doctor if

DAYTIME

- nervousness, dizziness or sleeplessness occur
- pain, cough, and nasal congestion gets worse or lasts more than 7 days
- redness or swelling is present
- new symptoms occur
- fever gets worse or lasts more than 3 days
- cough comes back or occurs with rash or headache that lasts

These could be signs of a serious condition.

NIGHTTIME

- pain or cough gets worse or lasts more than 7 days
- fever gets worse or lasts more than 3 days
- redness or swelling is present
- new symptoms occur
- cough comes back or occurs with rash headache that lasts.

These could be a signs of a serious condition.

If pregnant or breast-feeding,

ask a health professional before use.

Keep out of reach of children.

Overdose warning: Taking more than the recommended dose can cause liver damage. In case of overdose, get medical help or contact a Poison Control Center (1-800-222-1222) right away. Quick medical attention is critical for adults as well as for children even if you do not notice any signs or symptoms.

Directions

DAYTIME

- do not take more than directed (see Overdose warning)
- do not take more than 4 doses in 24 hours
- swallow whole; do not crush, chew, or dissolve
- adults and children 12 years and over: take 2 softgels with water every 4 hours.
- children under 12 years: do not use

NIGHTTIME

- do not take more than directed (see Overdose warning)
- do not take more than 4 doses in 24 hours
- swallow whole; do not crush, chew, or dissolve
- adults and children 12 years and over: take 2 softgels with water every 6 hours
- children under 12 years: do not use

Other information

- store between 15-30°C (59-86°F)
- avoid excessive heat

Inactive ingredients

DAYTIME

FD&C red #40, FD&C yellow #6, gelatin, glycerin, lecithin, light mineral oil, mannitol, polyethylene glycol, povidone, propylene glycol, purified water, sorbitan, sorbitol, white ink

NIGHTTIME

D&C yellow #10, FD&C blue #1, gelatin, glycerin, lecithin, light mineral oil, mannitol, polyethylene glycol, povidone, propylene glycol, purified water, sorbitan, sorbitol, white ink

Questions or comments?

Call 1-800-824-1706 Monday-Friday 9AM-4PM MST

Principal Display Panel

†Compare to the active ingredients in VICKS® DAYQUIL™ & NYQUIL™ LiquiCap™

Daytime

ACETAMINOPHEN/

PAIN RELIEVER - FEVER REDUCER

DEXTROMETHORPHAN HBr/ COUGH SUPPRESSANT

PHENYLEPHRINE HCI/ NASAL DECONGESTANT

Relieves: Aches, Fever, Sore Throat, Cough, Nasal Congestion & Sinus Pressure

Nighttime

ACETAMINOPHEN /

PAIN RELIEVER - FEVER REDUCER

DEXTROMETHORPHAN HBr / COUGH SUPPRESSANT

DOXYLAMINE SUCCINATE / ANTIHISTAMINE

Relieves: Aches, Fever, Sore Throat, Cough, Sneezing & Runny Nose

Softgels**

**Liquid-filled capsules

When using Daytime and Nighttime products, carefully read the labeling to ensure correct dosing

†This product is not manufactured or distributed by The Procter & Gamble Company. Vicks®, DayQuil™, NyQuil™, and LiquiCaps™ are registered

trademarks of the Procter and Gamble Company.

TAMPER EVIDENT: DO NOT USE IF CARTON IS OPENED OR IF BLISTER UNIT IS TORN, BROKEN OR SHOW SIGNS OF TAMPERING.

KEEP OUTER CARTON FOR COMPLETE WARNINGS AND PRODUCT INFORMATION.

DISTRIBUTED BY:

WINCO FOODS, LLC,

BOISE, ID 83704

Product Label

WINCO FOODS Daytime Nighttime Multi-Symptom Cold & Flu Relief